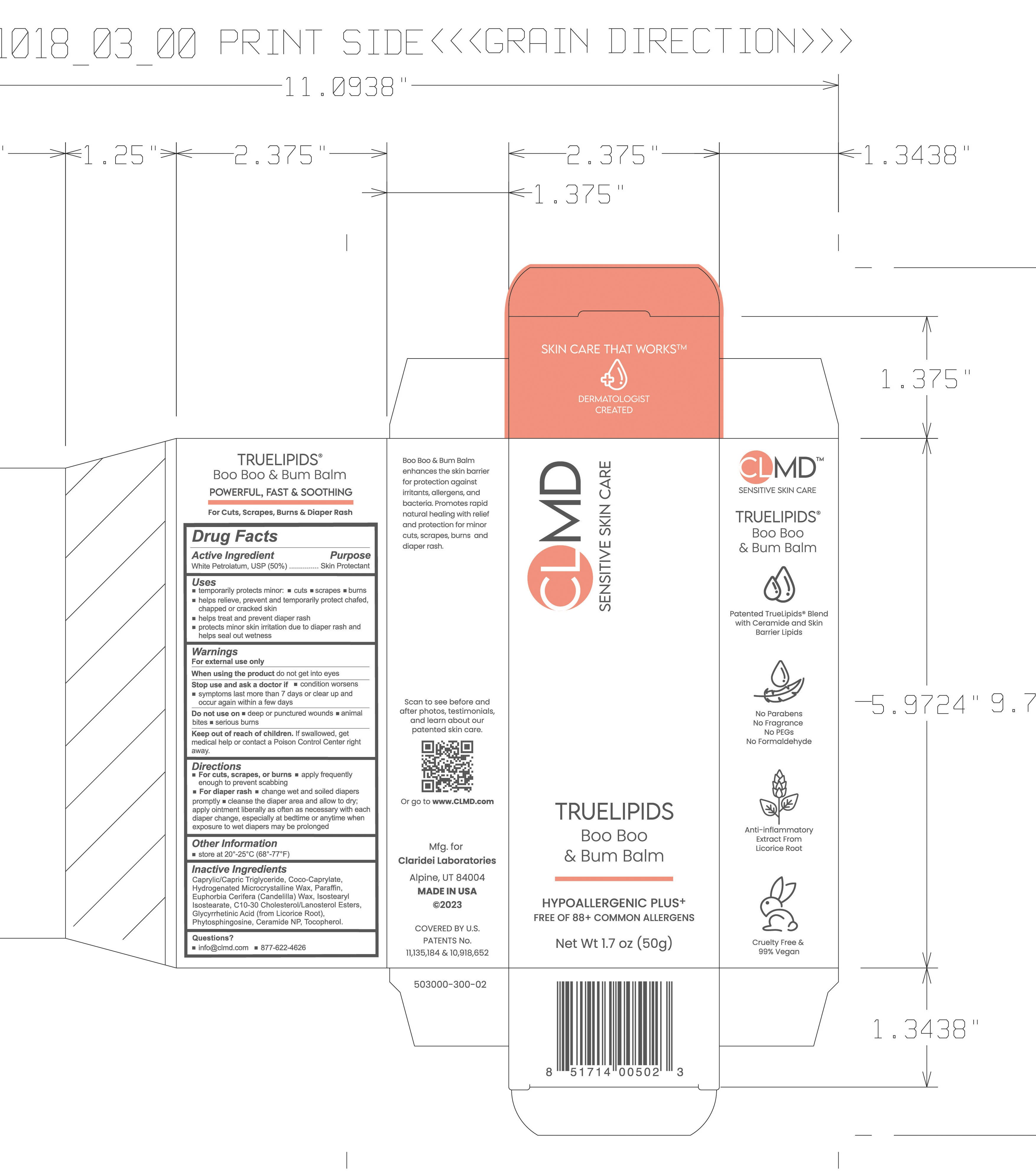 DRUG LABEL: TrueLipids Boo-Boo and Bum Balm
NDC: 61387-253 | Form: OINTMENT
Manufacturer: Claridei Laboratories, Inc.
Category: otc | Type: HUMAN OTC DRUG LABEL
Date: 20251215

ACTIVE INGREDIENTS: PETROLATUM 50 g/100 g
INACTIVE INGREDIENTS: C10-30 CHOLESTEROL/LANOSTEROL ESTERS; MEDIUM-CHAIN TRIGLYCERIDES; COCO-CAPRYLATE; CANDELILLA WAX; ENOXOLONE; ISOSTEARYL ISOSTEARATE; MICROCRYSTALLINE WAX; PARAFFIN; PHYTOSPHINGOSINE; TOCOPHEROL; CERAMIDE NP

TrueLipids Boo-Boo and Bum Balm

Active Ingredient Purpose

White Petrolatum 50% Skin Protectant

Uses

- temporarily protects minor:
- cuts
- scrapes
- burns
- helps relieve, prevent and temporarily protect chafed, chapped or chracked skin.
- helps treat and prevent diaper rash
- protects minor skin irritation due to diaper rash and helps seal out wetness

Keep out of reach of children. If swallowed, get medical help or contact a Poison Control Center right away.

Stop use and ask a doctor if
condition worsens
symptoms last more than 7 days or clear up and occur again within a few days

Warnings

For external use only

When using this product:

- do not get into eyes

Do not use on:

- deep or puncture wounds
- animal bites
- serious burns

Directions

- For cuts, scrapes or burns.
- apply as needed
- For diaper rash
- change wet and soiled diapers promptly
- cleanse the diaper area and allow to dry
- pply ointment liberally as often as necessary, with each diaper change, especially at bedtime or anytime when exposure to wet diapers may be prolonged.

Inactive Ingredients:

Carpylic/Capric Triglyceride, Coco-Caprlyate, Microcrystalline Wax, Paraffin, Euphorbia Cerifera (Candililla) Wax, C10-C30 Cholesterol/Lanosterol Esters, Isostearyl Isostearate, Glycyrrhetinic Acid(Licorice Root), Phytosphingosine, Ceramide NP, Tocopherol

PACKAGE LABEL

True Lipids Boo- Boo & Bum Balm

Net. Wt. 1.7 oz 50 g